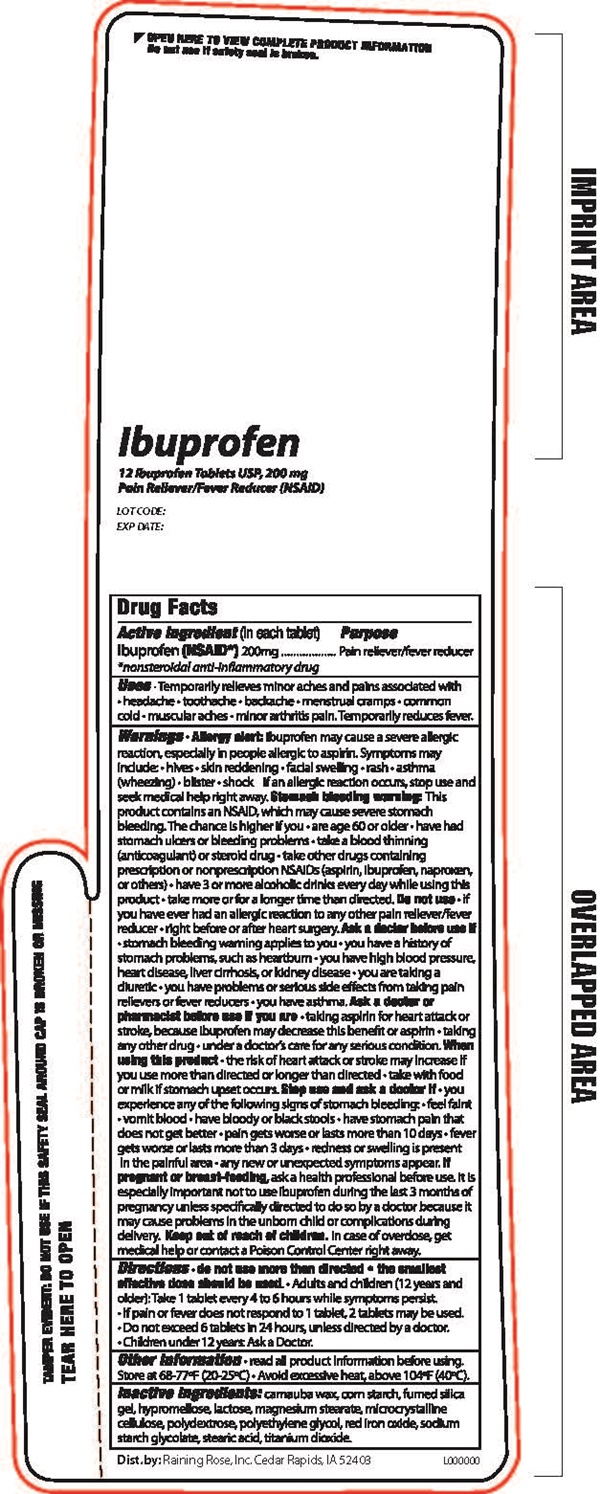 DRUG LABEL: IBUPROFEN
NDC: 65692-0412 | Form: TABLET, FILM COATED
Manufacturer: Raining Rose Inc.
Category: otc | Type: HUMAN OTC DRUG LABEL
Date: 20191105

ACTIVE INGREDIENTS: IBUPROFEN 200 mg/1 1
INACTIVE INGREDIENTS: CARNAUBA WAX; STARCH, CORN; HYPROMELLOSES; FERRIC OXIDE RED; LACTOSE; MAGNESIUM STEARATE; CELLULOSE, MICROCRYSTALLINE; POLYDEXTROSE; POLYETHYLENE GLYCOl; SILICON DIOXIDE; SODIUM STARCH GLYCOLATE TYPE A POTATO; STEARIC ACID; TITANIUM DIOXIDE

Ibuprofen - 0412

Drug Facts Active ingredient

Active ingredient (in each tablet)

Ibuprofen (NSAID)* 200 mg

*nonsteroidal anti-inflammatory drug

Purpose

Pain reliever/fever reducer

Keep out of reach of children. In case of overdose, get medical help or contact a Poison Control Center right away.

Uses

• Temporarily relieves minor aches and pains associated with • headache • toothache • backache • menstrual cramps • common cold • muscular aches • minor arthritis pain • Temporarily reduces fever.

Warnings Allergy Alert:

Ibuprofen may cause a severe allergic reaction, especially in people allergic to aspirin. Symptoms may include:

• hives • skin reddening • facial swelling • rash • asthma (wheezing) • blister • shock If an allergic reaction occurs, stop use and seek medical help right away.

Stomach bleeding warning: This product contains an NSAID, which may cause severe stomach bleeding. The chance is higher if you: • are age 60 or older • have had stomach ulcers or bleeding problems • take a blood thinner (anticoagulant) or steroid drug • take other drugs containing prescription or nonprescription NSAIDs (asprin, ibuprofen, naproxen, or others) • have 3 or more alcoholic drinks every day while using this product • take more or for a longer time than directed.

Do not use

• if you have ever had an allergic reaction to any other pain reliever/fever reducer • right before or after heart surgery

Ask a doctor before use if

• stomach bleeding warning applies to you • you have a history of stomach problems such as heartburn • you have high blood pressure, heart disease, liver cirrhosis, or kidney disease • you are taking a diuretic • you have problems or serious side effects from taking pain relivers or fever reducers • you have asthma

Ask a doctor or pharmacist before use if you are

• taking aspirin for heart attack or stroke, because ibuprofen may decrease the benefit or aspirin • taking any other drug • under a doctor's care for any serious condition

When using this product

• the risk of a heart attack or stroke may increase if you use more than directed or longer than directed • take with food or milk if stomach upset occurs

Stop use and ask a doctor if

• you experience any of the following signs of stomach bleeding: • feel faint • vomit blood • have bloody or blackstools • have stomach pain that does not get better • pain gets worse or lasts more than 10 days • fever gets worse or lasts more than 3 days • redness or swelling is present in the painful area • any new or unexpected symptoms appear.

If pregnant or breast-feeding,

ask a health professional before use. It is especially important not to use ibuprofen during the last 3 months of pregnancy unless specifically directed to do so by a doctor because it may cause problems in the unborn child or complications during delivery.

Directions

• do not use more than directed • the smallest effective dose should be used • Adults and children (12 years and older): Take 1 tablet every 4 to 6 hours while symptoms persist. • If pain or fever does not respond to 1 tablet, 2 tablets may be used. • Do not exceed 6 tablets in 24 hours, unless directed by a doctor. • Children under 12 years: Do not give to children under 12 years of age.

Inactive ingredients:

carnauba wax, corn starch, fumed silia gel, hypromellose, lactose, magnesium stearate, microcrystalline cellulose, polydextrose, polyethylene glycol, red irion oxide, sodium starch glycolate, stearic acid, titanium dioxide.

Other Information

• read all product information before using.

Store at 68-77°F (20-25°C) • Avoid ecessive heat, above 104°F (40°C).

Ibuprofen product label

IBUPROFEN

12 Ibuprofen Tablets USP, 200 mPain Reliever/Fever Reducer (NSAID)

LOT CODE:

EXP DATE:

OPEN HERE TO VIE COMPLETE PRODUCT INFORMATION

Do not use if safety seal is broken.

TAMPER EVIDENT: DO NOT USE IF THIS SAFETY SEAL AROUND CAP IS BROKEN OR MISSING

TEAR HERE TO OPEN

Dist. By Raining Rose, Inc. Cedar Rapids, IA 52403

L0000000

res